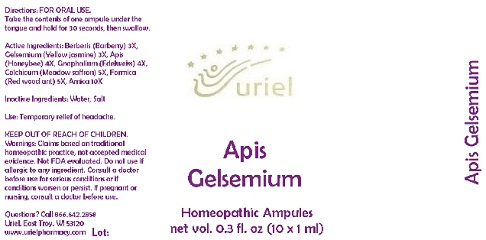 DRUG LABEL: Apis Gelsemium
NDC: 48951-1057 | Form: LIQUID
Manufacturer: Uriel Pharmacy Inc.
Category: homeopathic | Type: HUMAN OTC DRUG LABEL
Date: 20180416

ACTIVE INGREDIENTS: BERBERIS VULGARIS ROOT BARK 3 [hp_X]/1 mL; GELSEMIUM SEMPERVIRENS ROOT 3 [hp_X]/1 mL; APIS MELLIFERA 4 [hp_X]/1 mL; PSEUDOGNAPHALIUM LUTEOALBUM LEAF 4 [hp_X]/1 mL; COLCHICUM AUTUMNALE FLOWER 5 [hp_X]/1 mL; FORMICA RUFA 5 [hp_X]/1 mL; ARNICA MONTANA ROOT 10 [hp_X]/1 mL
INACTIVE INGREDIENTS: WATER; SODIUM CHLORIDE

Apis Gelsemium

INDICATIONS AND USAGE

Directions: FOR ORAL USE ONLY.

DOSAGE AND ADMINISTRATION

Take the contents of one ampule
under the tongue and hold for
30 seconds, then swallow.

ACTIVE INGREDIENT

Active Ingredients: Berberis (Barberry) 3X, Gelsemium (Yellow jasmine) 3X, Apis (Honeybee) 4X, Gnaphalium (Edelweiss) 4X, Colchicum (Meadow saffron) 5X, Formica (Red wood ant) 5X, Arnica 10X

Inactive Ingredients: Water, Salt

PURPOSE

Use: Temporary relief of headache.

KEEP OUT OF REACH OF CHILDREN.

WARNINGS

Warnings: Claims based on traditional homeopathic practice, not accepted medical evidence. Not FDA evaluated. Do not use if allergic to any ingredient. Consult a doctor before use for serious conditions or if conditions worsen or persist. If pregnant or nursing, consult a doctor before use.

Questions? Call 866.642.2858
Uriel, East Troy, WI 53120
www.urielpharmacy.com